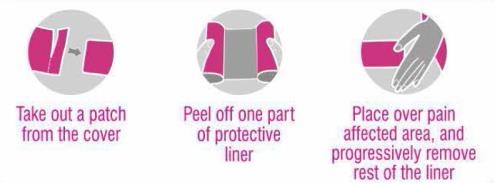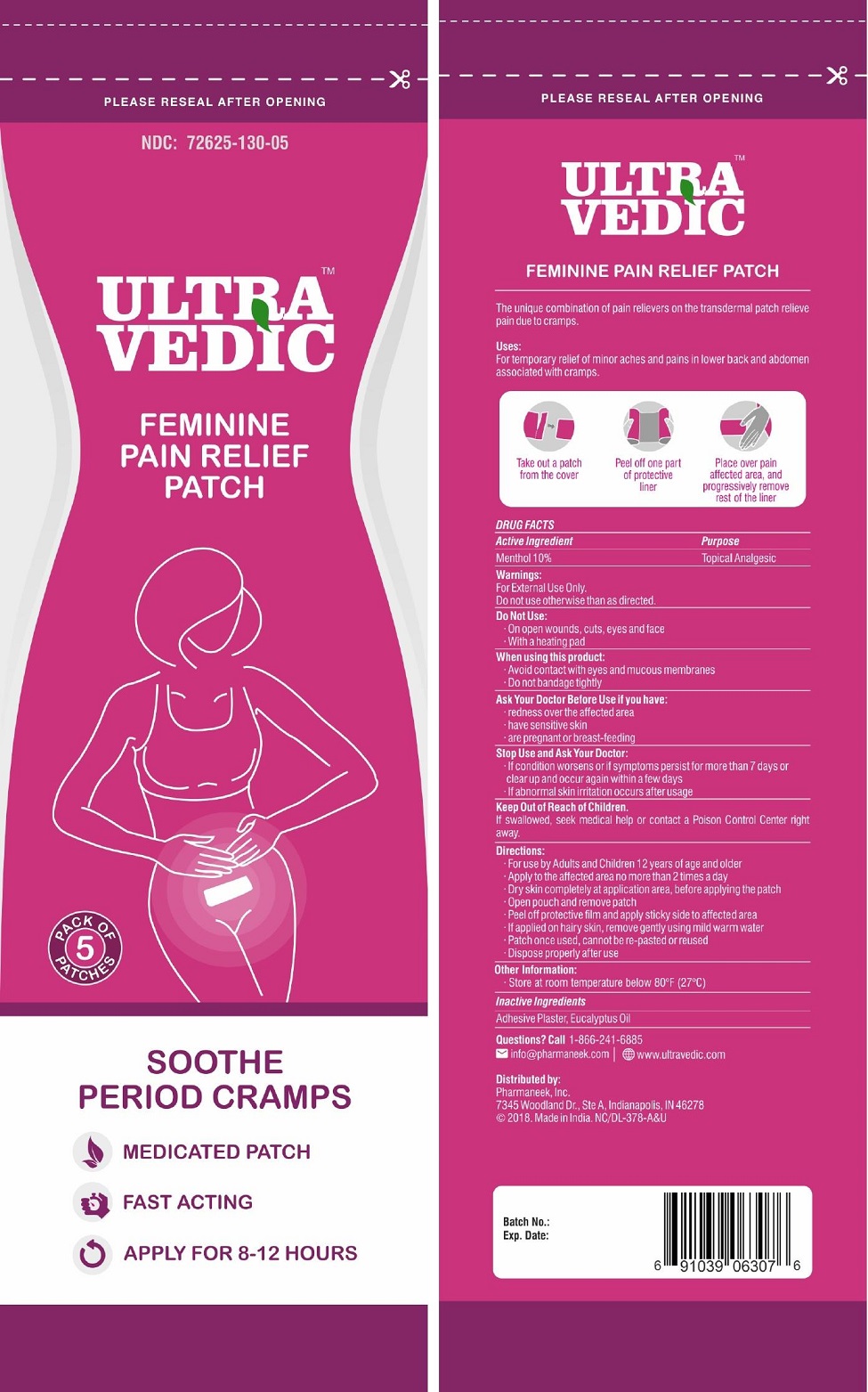 DRUG LABEL: Ultra Vedic
NDC: 72625-130 | Form: PATCH
Manufacturer: Pharmaneek, Inc.
Category: otc | Type: HUMAN OTC DRUG LABEL
Date: 20230118

ACTIVE INGREDIENTS: MENTHOL, UNSPECIFIED FORM 200 mg/1 1
INACTIVE INGREDIENTS: EUCALYPTUS OIL

Ultra Vedic TM

Feminine Pain Relief Patch

The unique combination of pain relievers on the transdermal patch relieve pain due to cramps.

Active Ingredient

Menthol 10%

Purpose

Topical Analgesic

Uses

For temporary relief of minor aches and pains in lower back and abdomen associated with cramps.

Warnings

For External Use Only

Do not use otherwise than as directed.

Do not use

- On open wounds, cuts, eyes, and face
- With a heating pad

When using this product

- Avoid contact with eyes and mucous membranes
- Do not bandage tightly

Ask Your Doctor Before Use if you have

- redness over the affected area
- have sensitive skin
- are pregnant or breast-feeding

Stop Use and Ask Your Doctor

- If condition worsens or if symptoms persist for more than 7 days or clear up and occur again within a few days
- If abnormal skin irritation occurs after usage

KEEP OUT OF REACH OF CHILDREN

If swallowed, seek medical help or contact a Poison Control Center right away.

Directions

- For use by Adults and Children 12 year of age and older
- Apply to the affected area no more than 2 times a day
- Dry skin completely at application site area, before applying the patch
- Open pouch and remove patch
- Peel off protective film and apply sticky side to affected area
- If applied on hairy skin, remove gently using mild warm water
- Patch once used cannot be re-pasted or reused
- Dispose properly after use

Other Information

- Store at room temperature below 80°F (27°C)

Inactive Ingredients

Adhesive Plaster, Eucalyptus Oil

Questions?

Call 1-866-241-6885
info@pharmaneek.com
www.ultravedic.com

Distributed by:
Pharmaneek, Inc.
7345 Woodland Dr., Ste A,
Indianapolis, IN 46278
© 2018. Made in India. NC/DL-378-A&U

PACKAGE LABEL.PRINCIPAL DISPLAY PANEL

Please Reseal After Opening

NDC: 72625-130-05

ULTRA VEDIC

Feminine Pain Relief Patch

Pack of 5 Patches
Soothe Period Cramps
Medicated Patch
Fast Acting
Apply for 8-12 Hours